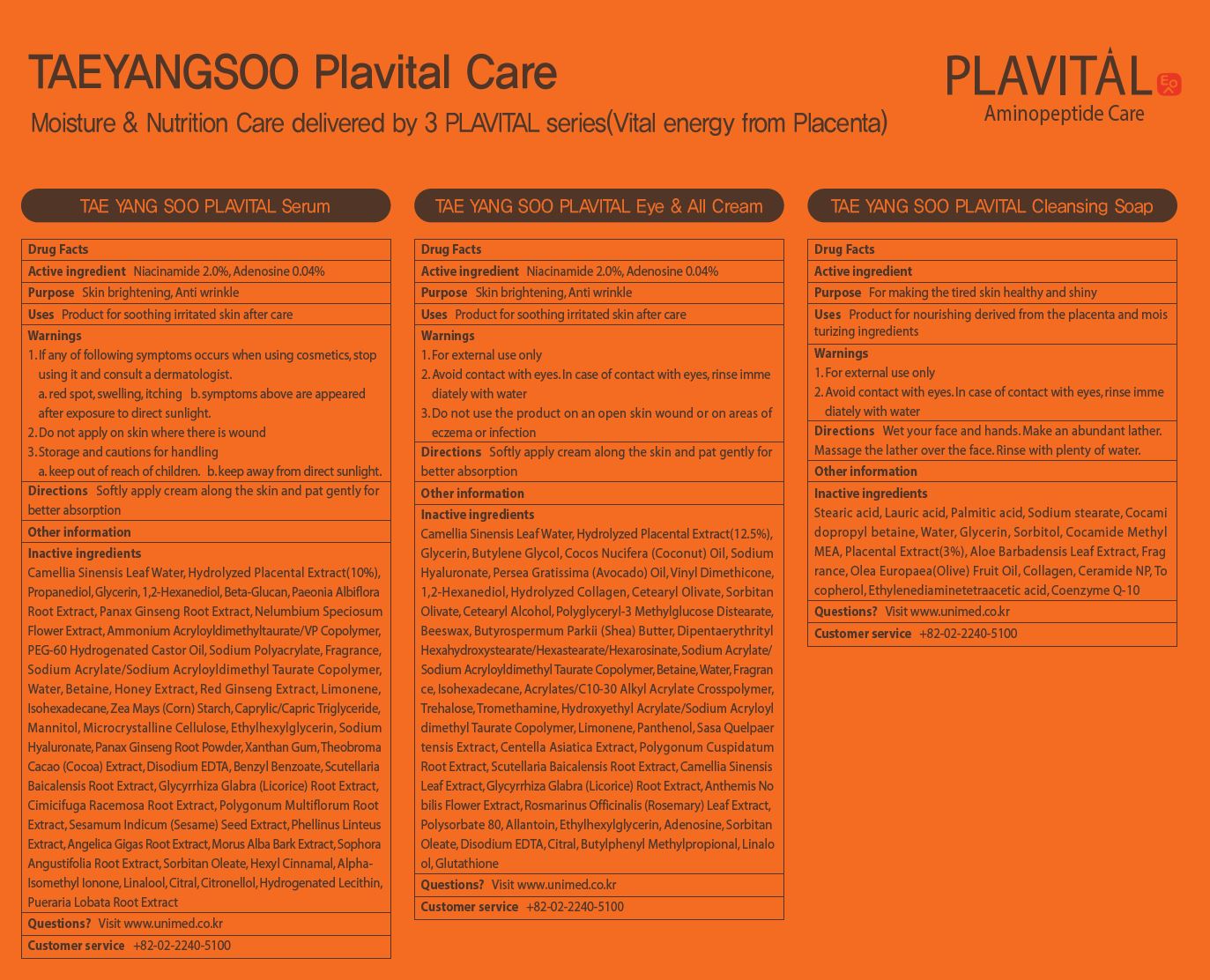 DRUG LABEL: TAEYANGSOO PLAVITAL EYE ALLCream
NDC: 73669-007 | Form: LIQUID
Manufacturer: Unimed Pharmaceuticals, Inc.
Category: otc | Type: HUMAN OTC DRUG LABEL
Date: 20210403

ACTIVE INGREDIENTS: NIACINAMIDE 2 g/100 mL; ADENOSINE 0.04 g/100 mL
INACTIVE INGREDIENTS: WATER

Drug Facts

ACTIVE INGREDIENT

adenosine, niacinamide

INACTIVE INGREDIENT

Camellia Sinensis Leaf Water, Hydrolyzed Placental Extract(12.5%),
Glycerin, Butylene Glycol, Cocos Nucifera (Coconut) Oil, Sodium
Hyaluronate, Persea Gratissima (Avocado) Oil, Vinyl Dimethicone,
1,2-Hexanediol, Hydrolyzed Collagen, Cetearyl Olivate, Sorbitan
Olivate, Cetearyl Alcohol, Polyglyceryl-3 Methylglucose Distearate,
Beeswax, Butyrospermum Parkii (Shea) Butter, Dipentaerythrityl
Hexahydroxystearate/Hexastearate/Hexarosinate, Sodium Acrylate/
Sodium Acryloyldimethyl Taurate Copolymer, Betaine, Water, Fragran
ce, Isohexadecane, Acrylates/C10-30 Alkyl Acrylate Crosspolymer,
Trehalose, Tromethamine, Hydroxyethyl Acrylate/Sodium Acryloyl
dimethyl Taurate Copolymer, Limonene, Panthenol, Sasa Quelpaer
tensis Extract, Centella Asiatica Extract, Polygonum Cuspidatum
Root Extract, Scutellaria Baicalensis Root Extract, Camellia Sinensis
Leaf Extract, Glycyrrhiza Glabra (Licorice) Root Extract, Anthemis No
bilis Flower Extract, Rosmarinus Officinalis (Rosemary) Leaf Extract,
Polysorbate 80, Allantoin, Ethylhexylglycerin, Adenosine, Sorbitan
Oleate, Disodium EDTA, Citral, Butylphenyl Methylpropional, Linalo
ol, Glutathione

PURPOSE

Skin brightening, Anti wrinkle

keep out of reach of the children

INDICATIONS AND USAGE

Softly apply cream along the skin and pat gently for better absorption

WARNINGS

1. For external use only
2. Avoid contact with eyes. In case of contact with eyes, rinse imme
diately with water
3. Do not use the product on an open skin wound or on areas of
eczema or infection

DOSAGE AND ADMINISTRATION

external use only